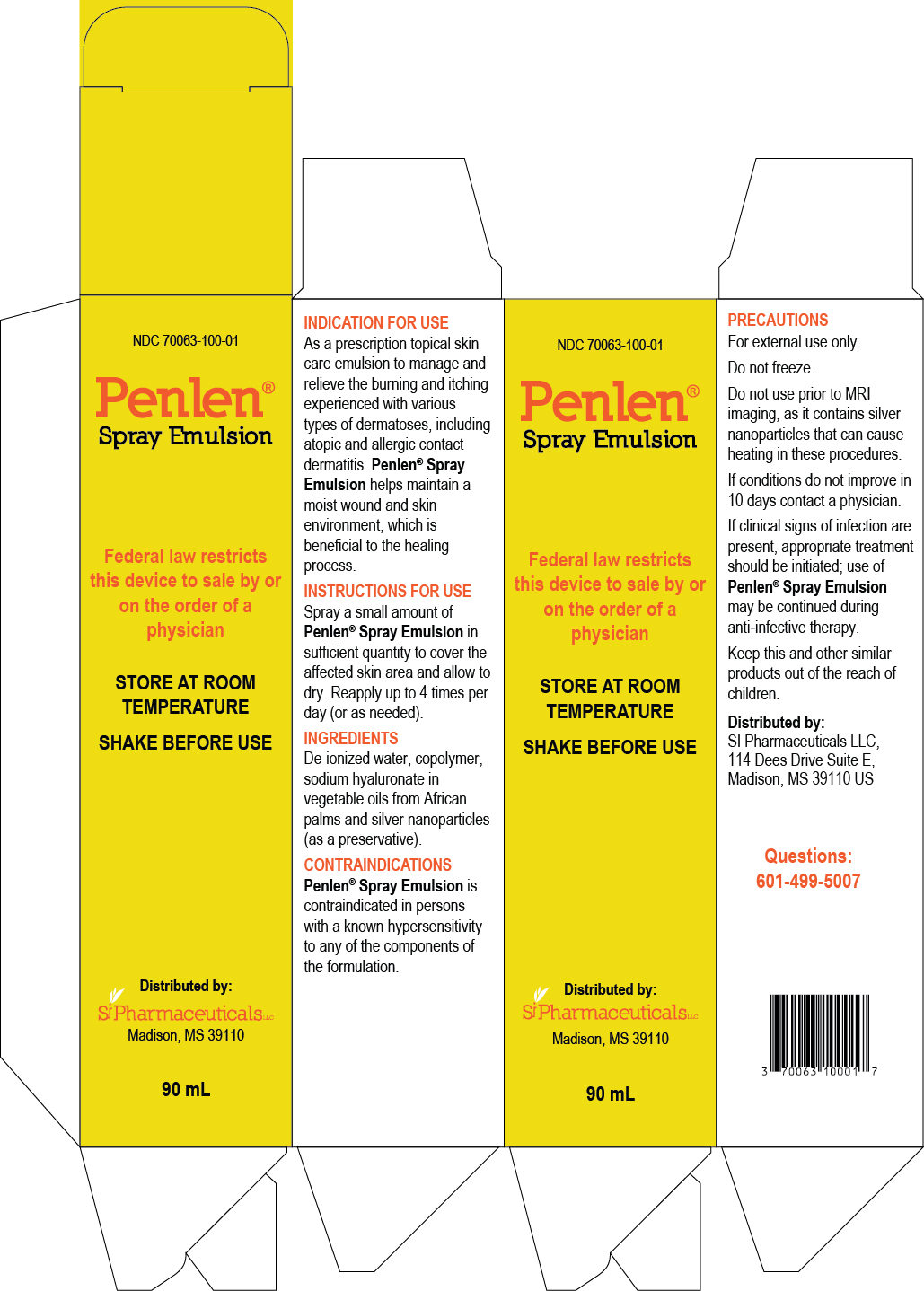 DRUG LABEL: Penlen Spray Emulsion
NDC: 70063-100
Manufacturer: SI Pharmaceuticals LLC
Category: other | Type: PRESCRIPTION MEDICAL DEVICE LABEL
Date: 20181204

Penlen® Spray Emulsion
Penlen Spray Emulsion 90 mL (NDC 70063-100-01)
For Topical Dermatological Use only.Rx Only

DESCRIPTION

Penlen® Spray Emulsion is a water-based topical skin care emulsion that is indicated to manage and relieve the burning and itching experienced with various types of dermatoses, including atopic and allergic contact dermatitis.

Penlen® Spray Emulsion contains natural extracts to moisturize the skin.

INDICATIONS & USAGE

As a prescription topical skin care emulsion to manage and relieve the burning and itching experienced with various types of dermatoses, including atopic and allergic contact dermatitis.

Penlen® Spray Emulsion helps maintain a moist wound and skin environment, which is beneficial to the healing process.

CONTRAINDICATIONS

Penlen Spray Emulsion is contraindicated in persons with a known hypersensitivity to any of the components of the formulation

PRECAUTIONS

Penlen® Spray Emulsion is for external use only.

Product should not be used prior to MRI Imaging, as it contains silver nanoparticles that can cause heating during these procedures.

Penlen® Spray Emulsion does not contain sunscreen.

If the condition does not improve within 10 days, consult a physician.

If clinical signs of infection are present, appropriate treatment should be initiated; use of Penlen® Spray Emulsion may be continued during anti-infective therapy.

Keep this and other similar products out of the reach of children.

DIRECTIONS FOR USE

Spray a small amount of Penlen® Spray Emulsion in sufficient quantity to cover the affected skin area to be protected, and allow to dry. Reapply up to 4 times per day (or as needed).

INGREDIENTS

De-ionized water, copolymer, sodium hyaluronate in vegetable oils from African palms and silver nanoparticles (as a preservative).

HOW SUPPLIED

Penlen® Spray Emulsion is available in a 90 mL spray bottle.

PRESCRIPTION MEDICAL DEVICE: FEDERAL LAW RESTRICTS THIS DEVICE TO SALE BY OR ON THE ORDER OF A PHYSICIAN

STORAGE AND HANDLING

STORE AT ROOM TEMPERATURE

SHAKE WELL BEFORE USING

Distributed in the U.S.A. by:

SI Pharmaceuticals LLC
Madison, MS 39110

Manufactured by: Laboratorios Zepol S.A. Costa Rica

FDA approval: K141637

Container Label

Penlen® Spray Emulsion 90 mL (NDC 70063-100-01)
For Topical Dermatological Use only.
Rx Only